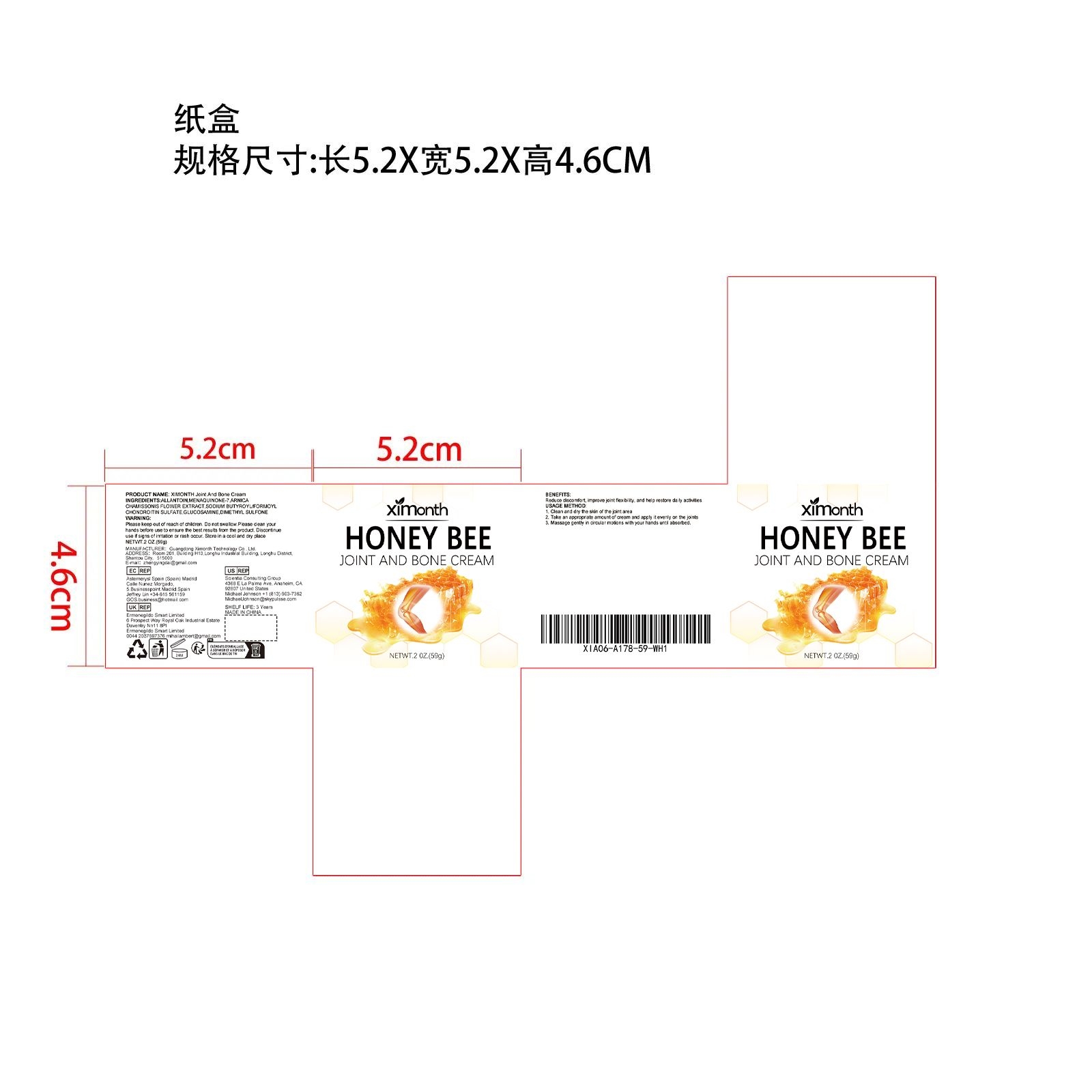 DRUG LABEL: Joint And Bone Cream
NDC: 84660-013 | Form: CREAM
Manufacturer: Guangdong Ximonth Technology Co., Ltd.
Category: otc | Type: HUMAN OTC DRUG LABEL
Date: 20240909

ACTIVE INGREDIENTS: MENAQUINONE 7 11.8 g/59 g; ARNICA CHAMISSONIS FLOWER 5.9 g/59 g; DIMETHYL SULFONE 5.9 g/59 g; GLUCOSAMINE 8.85 g/59 g
INACTIVE INGREDIENTS: SODIUM BUTYROYL/FORMOYL HYALURONATE 8.85 g/59 g; ALLANTOIN 17.7 g/59 g

Active Ingredient(s)

MENAQUINONE-7、ARNICA CHAMISSONIS FLOWER EXTRACT、SODIUM BUTYROYL/FORMOYL CHONDROITIN SULFATE
、GLUCOSAMINE、DIMETHYL SULFONE

Purpose

Reduce discomfort, improve joint flexibility, and help restore daily activities.

Use

1. Clean and dry the skin of the joint area. 2. Take an appropriate amount of cream and apply it evenly on the joints. 3. Massage gently in circular motions with your hands until absorbed.

Warnings

Please keep out of reach of children.Do not swallow.Please clean your hands before use to ensure the best results from the product.Discontinue use if signs of irritation or rash occur.Store in a cool and dry place.

Do not use

Discontinue use if signs of irritation or rash occur.

STOP USE

Discontinue use if signs of irritation or rash occur.

KEEP OUT OF REACH OF CHILDREN

Please keep out of reach of children. Do not swallow.

STORAGE AND HANDLING

Avoid freezing and excessive heat above 40C (104F) ）

Store in a cool and dry place.

INACTIVE INGREDIENT

ALLANTOIN